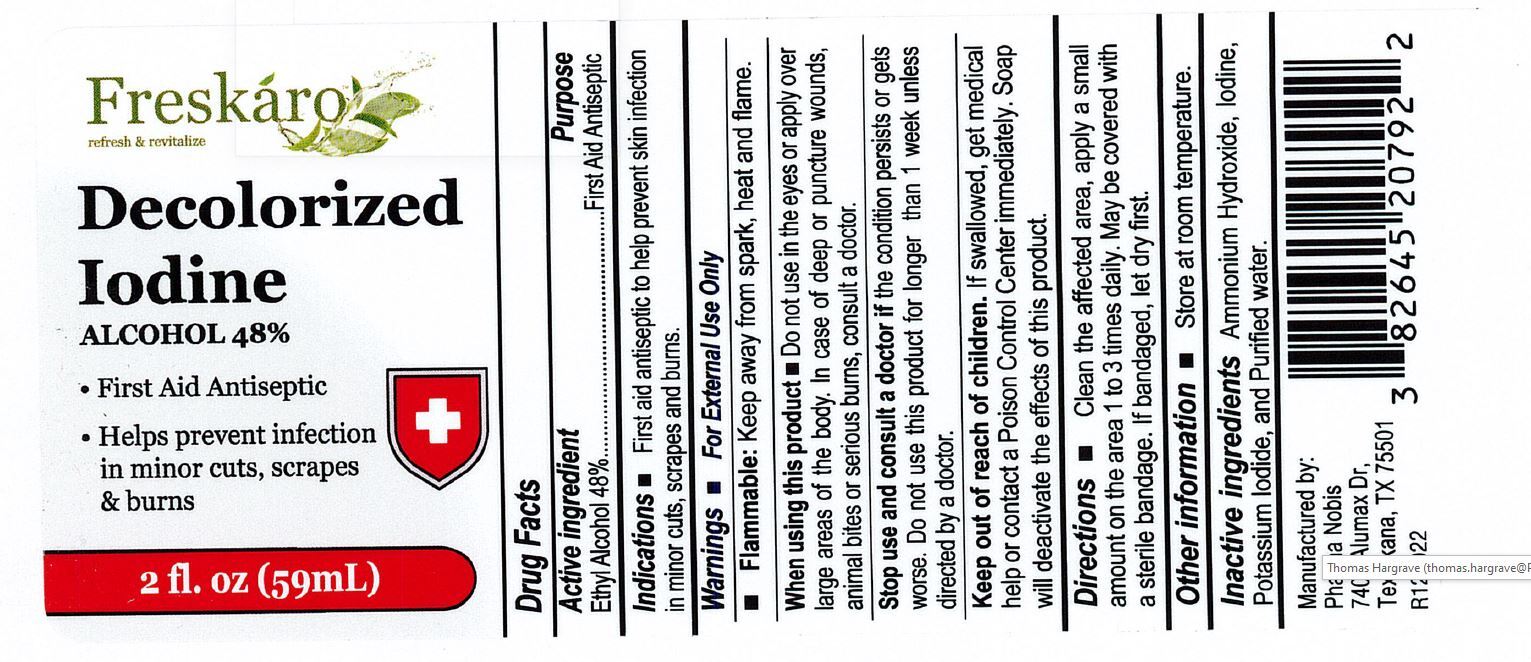 DRUG LABEL: Freskaro Decolorized Iodine
NDC: 82645-207 | Form: LIQUID
Manufacturer: Pharma Nobis, LLC
Category: otc | Type: HUMAN OTC DRUG LABEL
Date: 20231228

ACTIVE INGREDIENTS: ALCOHOL 0.48 mL/1 mL
INACTIVE INGREDIENTS: AMMONIA; IODINE; POTASSIUM IODIDE; WATER

Freskaro Decolorized Iodine

Freskaro Decolorized Iodine

Drug Facts

Active Ingredient

Alcohol 48%

Purpose

First Aid Antiseptic

Uses

First Aid Antiseptic to help prevent infection in in minor, cuts, scrapes and burns.

Warnings

For External Use Only

When using the product

Do not use in the eyes or apply over large areas of the bosy. In case of deep or puncture wounds, animal bites or serious burns, consult a doctor.

Stop use and consult a doctor if

the condition persists or gets worse. Do not use this product for longer than 1 week unless directed by a doctor.

Keep out of reach of children.

If swallowed, get medical help or contact a Poison Control Center immediately. Soap will deactivate the effects of this product.

Directions

- Clean the affected area. Apply a small amount to the affected area 1 to 3 times daily. May be covered with a sterile bandage. If bandaged, let dry first.

Inactive Ingredient

Ammonia Hydroxide, Iodine, Potassium Iodide, Purified water.

Other information

Flammable: Keep away from spark, heat and flame